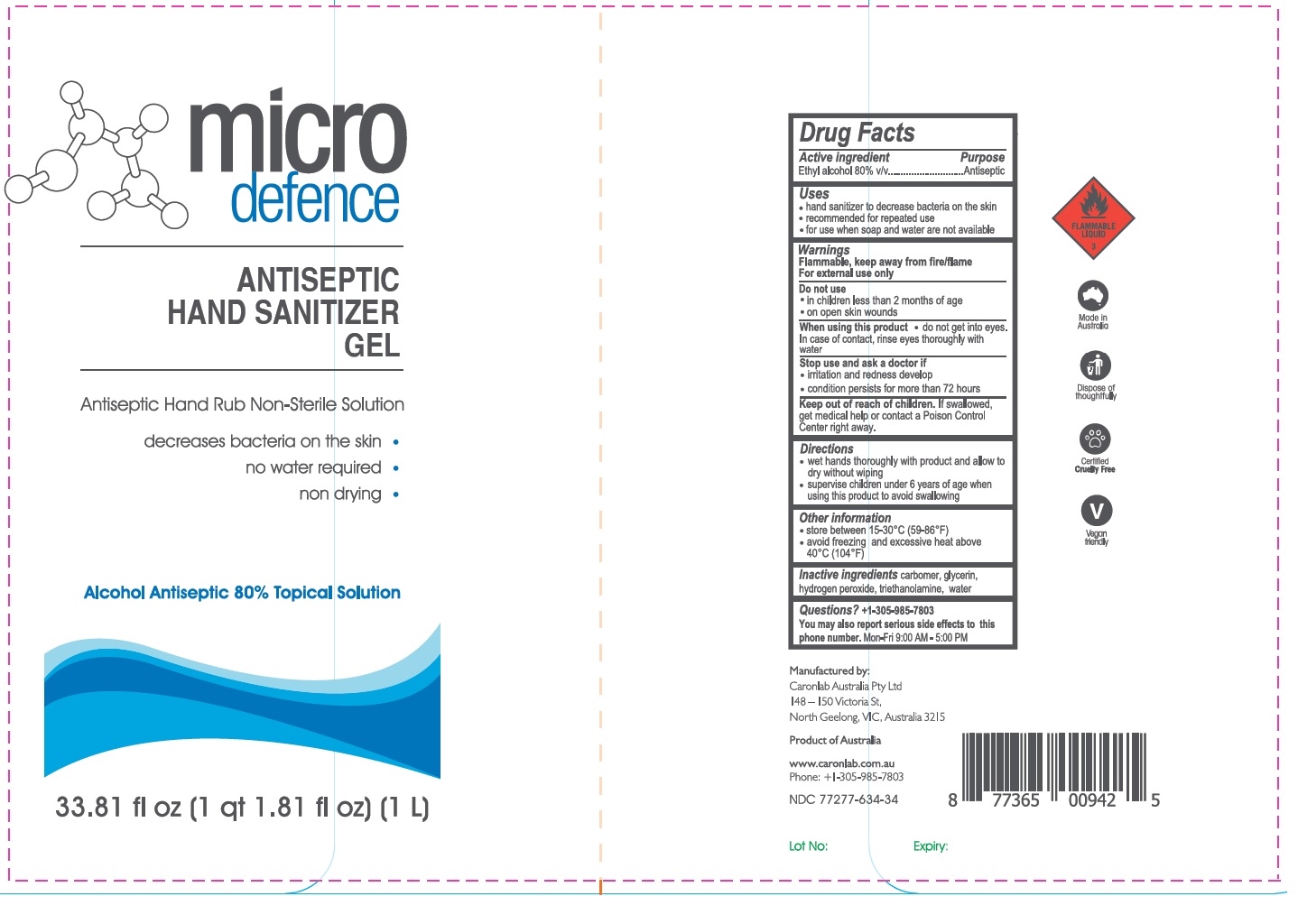 DRUG LABEL: Micro Defence Antiseptic Hand Sanitizer
NDC: 77277-634 | Form: GEL
Manufacturer: CARONLAB AUSTRALIA PTY LTD
Category: otc | Type: HUMAN OTC DRUG LABEL
Date: 20220119

ACTIVE INGREDIENTS: ALCOHOL 80 mL/100 mL
INACTIVE INGREDIENTS: CARBOMER HOMOPOLYMER, UNSPECIFIED TYPE; GLYCERIN; HYDROGEN PEROXIDE; TROLAMINE; WATER

micro defence ANTISEPTIC HAND SANITIZER GEL

Active ingredient

Ethyl alcohol 80% v/v

Purpose

Antiseptic

Uses

- hand sanitizer to decrease bacteria on the skin
- recommended for repeated use
- for use when soap and water are not available

Warnings

Flammable, keep away from fire/flame

For external use only
Do not use

- in children less than 2 months of age
- on open skin wounds

When using this product do not get into eyes. In case of contact, rinse eyes thoroughly with water
Stop use and ask a doctor if

- irritation and redness develop
- condition persists for more than 72 hours

Keep out of reach of children.

If swallowed, get medical help or contact a Poison Control Center right away.

Directions

- wet hands thoroughly with product and allow to dry without wiping
- supervise children under 6 years of age when using this product to avoid swallowing

Other information

- store between 15-30°C (59-86°F)
- avoid freezing and excessive heat above 40°C (104°F)

Inactive ingredients

carbomer, glycerin, hydrogen peroxide, triethanolamine, water

Questions?

+1-305-985-7803
You may also report serious side effects to this phone number. Mon-Fri 9:00 AM - 5:00 PM

Antiseptic Hand Rub Non-Sterile Solution

decreases bacteria on the skin

no water required

non drying

Alcohol Antiseptic 80% Topical Solution

Manufactured by:

Caronlab Australia Pty Ltd

148-150 Victoria St,

North Geelong, VIC, Australia 3215

Product of Australia

www.caronlab.com.au

Phone: +1+305-985-7803

Lot No:

Expiry:

FLAMMABLE LIQUID

Made in Australia

Dispose of thoughtfully

Certified Cruelty Free

Vegan friendly